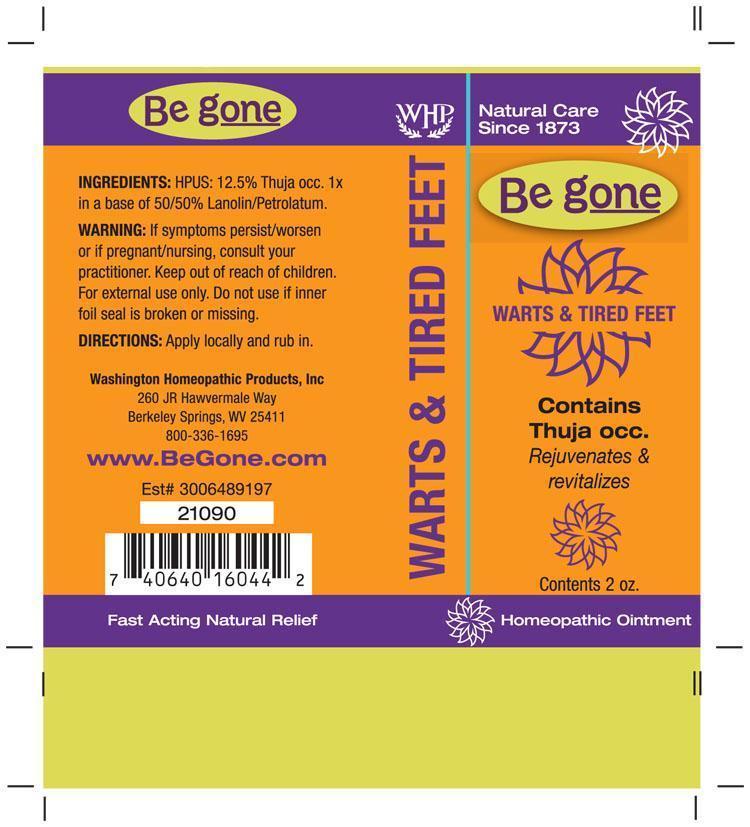 DRUG LABEL: Be gone Warts and Tired Feet
NDC: 68428-722 | Form: OINTMENT
Manufacturer: Washington Homeopathic Products
Category: homeopathic | Type: HUMAN OTC DRUG LABEL
Date: 20191223

ACTIVE INGREDIENTS: THUJA OCCIDENTALIS LEAFY TWIG 1 [hp_X]/56 g
INACTIVE INGREDIENTS: PETROLATUM; LANOLIN

DRUG FACTS

ACTIVE INGREDIENTS

THUJA OCCIDENTALIS 1X

USES

To relieve tired feet and skin conditions auch as warts, calluses and corns.

KEEP OUT OF REACH OF CHILDREN

Keep this and all medicines out of reach of children.

INDICATIONS

THUJA OCCIDENTALIS Warts

STOP USE AND ASK DOCTOR

For external use only. If symptoms persist/worsen or if pregnant/nursing, consult your practitioner. Do not use if inner foil seal is broken or missing.

DIRECTIONS

Apply locally and rub in.

INACTIVE INGREDIENTS

50% Lanolin

50% Petrolatum

PRINCIPAL DISPLAY PANEL

Be gone Warts & Tired Feet tube